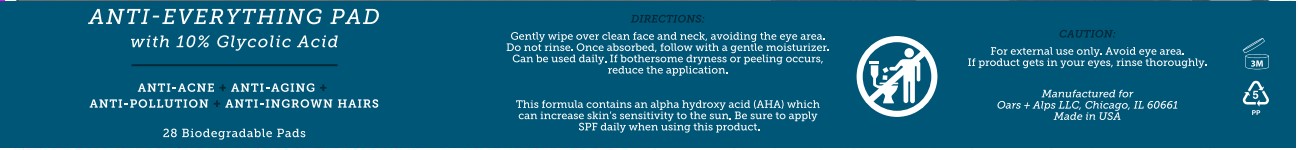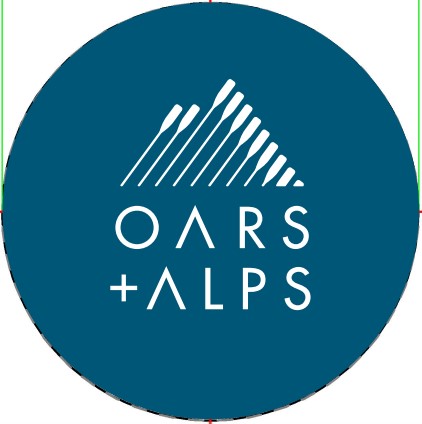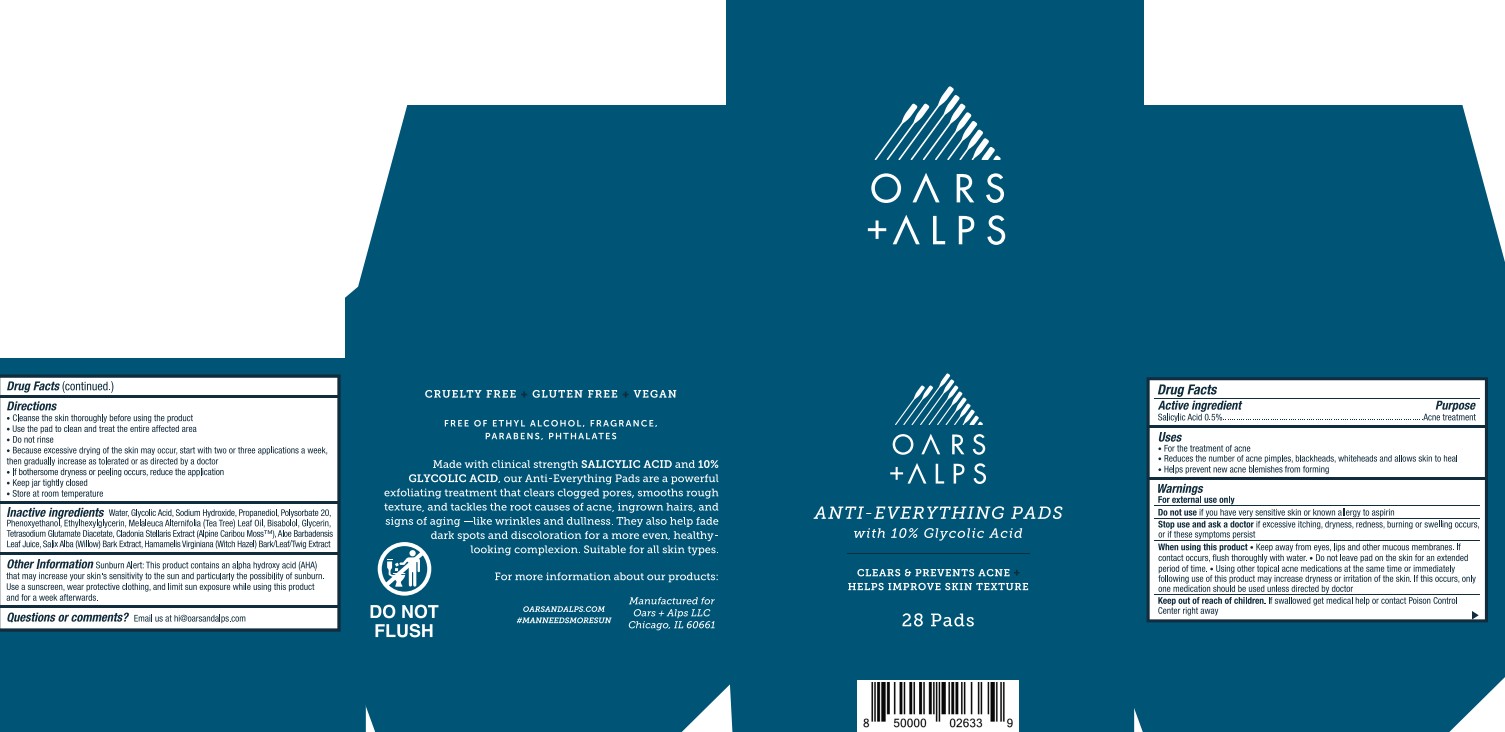 DRUG LABEL: Resurfacing acne swipes
NDC: 83046-100 | Form: SWAB
Manufacturer: Oars And Alps LLC
Category: otc | Type: HUMAN OTC DRUG LABEL
Date: 20251201

ACTIVE INGREDIENTS: SALICYLIC ACID 0.005 mg/1 mL
INACTIVE INGREDIENTS: LEVOMENOL; DIGLYCERIN; ALOE VERA LEAF; GLYCOLIC ACID; SALIX ALBA BARK; TETRASODIUM GLUTAMATE DIACETATE; WATER; HAMAMELIS VIRGINIANA TOP; CLADONIA RANGIFERINA WHOLE; SODIUM HYDROXIDE; PROPANEDIOL; POLYSORBATE 20; TEA TREE OIL; PHENOXYETHANOL; ETHYLHEXYLGLYCERIN

OARS+ALPS
Glycolic Acid Facial

Active Ingredient

Salicylic Acid 0.5%

Purpose

Acne treatment

Uses

- For the treatment of acne
- Reduces the number of acne pimples and blackheads
- Allows skin to heal
- Helps prevent new acne pimples from forming

Warnings

For external use only

Do not use if you have very sensitive skin or known allergy to aspirin

Stop use ask a doctor If excessive itching, dryness, redness, burning or swelling occurs, or if these symptoms persist

When using this product • Keep away from eyes, lips and other mucous membranes. If contact occurs, flush thoroughly with water. • Do not leave pad on the skin for an extended period of time. • Using other topical acne medications at the same time or immediately following use of this product may increase dryness or irritation of the skin. If this occurs, only one medication should be used unless directed by doctor

Keep out of reach of children

If swallowed get medical help or contact Poison Control Center right away

Directions

- Cleanse the skin thoroughly before using the product
- Use the pad to clean and treat the entire affected area one to three times daily
- Do not rinse
- Because excessive drying of the skin may occur, start with one application daily, then gradually increase if needed or as directed by a doctor
- If bothersome dryness or peeling occurs, reduce the application
- Keep jar tightly closed
- Store at room temperature

Inactive ingredients

Water, Glycolic Acid, Sodium Hydroxide, Propanediol, Polysorbate 20, Salix Alba (Willow) Bark Extract, Hamamelis Virginiana (Witch Hazel) Bark/Leaf/Twig Extract, Cladonia Stellaris Extract (Alpine Caribou Moss), Melaleuca Alternifolia (Tea Tree) Leaf Oil, Aloe Barbadensis Leaf Juice, Glycerin, Bisabolol, Tetrasodium Glutamate Diacetate, Phenoxyethanol, Ethylhexylglycerin

Other Information

Sunburn Alert: This product contains an alpha hydroxy acid (AHA) that may increase your skin’s sensitivity to the sun and particularly the possibility of sunburn. Use a sunscreen, wear protective clothing, and limit sun exposure while using this product and for a week afterwards.

Questions or comments

Email us at hi@oarsandalps.com, or call (630) 635-7839

Label

OARS+ALPS

ANTI- EVERYTHING PAD

With 10% Glycolic Acid

ANTI-AGNE +ANTI-AGING +

ANTI-POLLUTION + ANTI-INGROWN HAIRS

28 Biodegradable Pads

DIRECTIONS:

Gently wipe over clean face and neck, avoiding the eye area.

Do not rinse. Once absorbed, follow with a gentle moisturizer.

Can be used daily. If bothersome dryness or peeling occurs,

reduce the application.

This formula contains an alpha hydroxy acid (AHA) which can increase skin’s sensitivity to the sun. be sure to apply SPF daily when using this product.

CAUTION:

For external use only. Avoid Eye area.

If product gets in your eyes, rinse thoroughly.

Manufactured for

Oars + Alps LLC, Chicago, IL 60661

Made in USA

3M

5

PP

OARS+ALPS

ANTI- EVERYTHING PAD

With 10% Glycolic Acid

ANTI-AGNE +

ANTI-AGING +

ANTI-POLLUTION +

ANTI-INGROWN HAIRS

28 Biodegradable Pads

CRUELTY FREE + GLUTEN FREE + VEGAN

FREE OF ALCOHOL, FRAGRANCE

PARABENS, PHTHALATES, SULFATES

Our pads help clear your complexion and minimize the appearance of pores.

This plant based formula contains Glycolic Acid and Salicylic Acid for a gentle chemical exfoliation that help refresh your surface skin cell layer and energize your skin.

OARSANDALPS.COM

#TAKETOTHEOARS

DO NOT FLUSH

Manufactured for Oars + Alps LLC

Chicago, IL 60661

Made in USA

3M

8 50000 02633 9